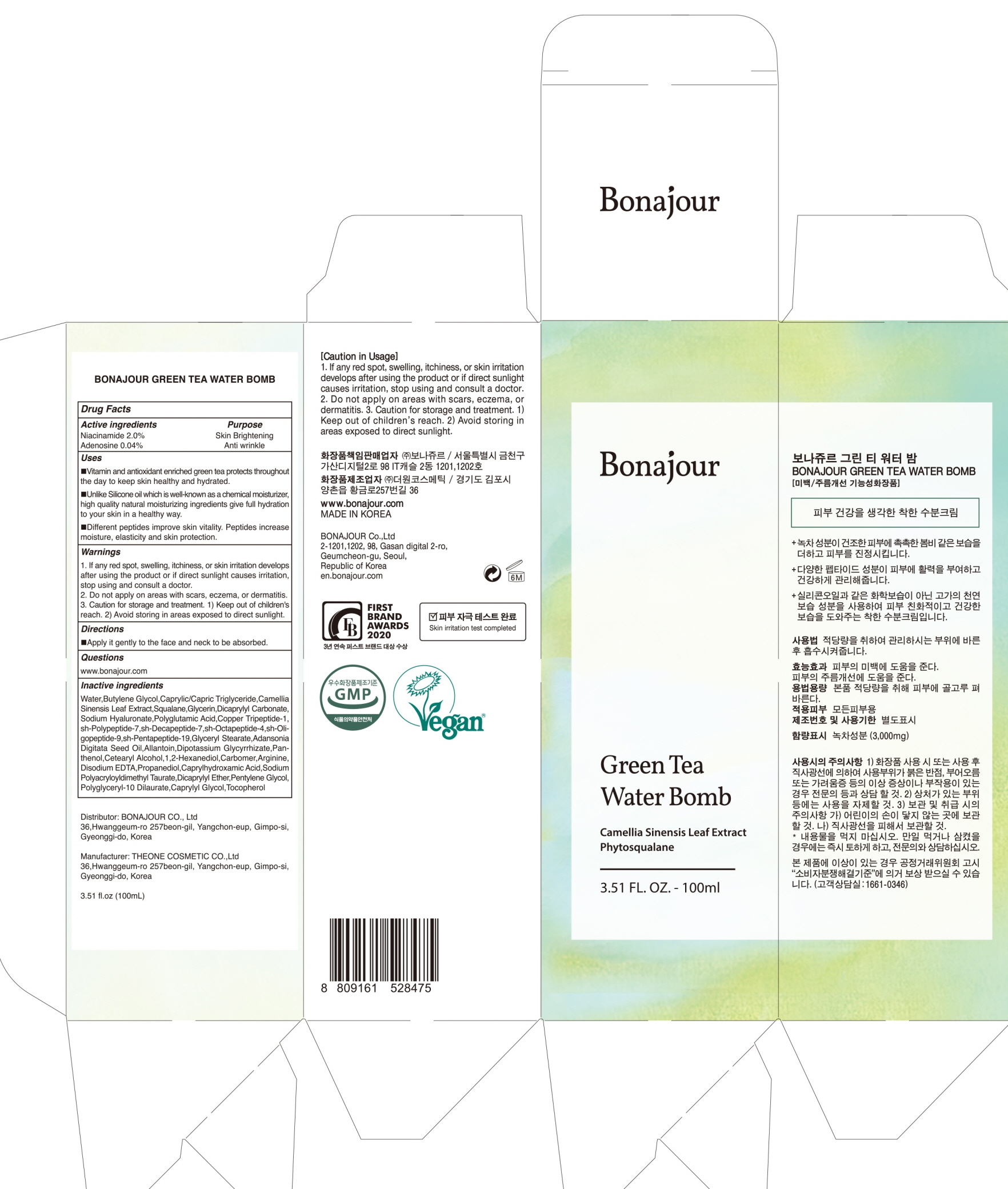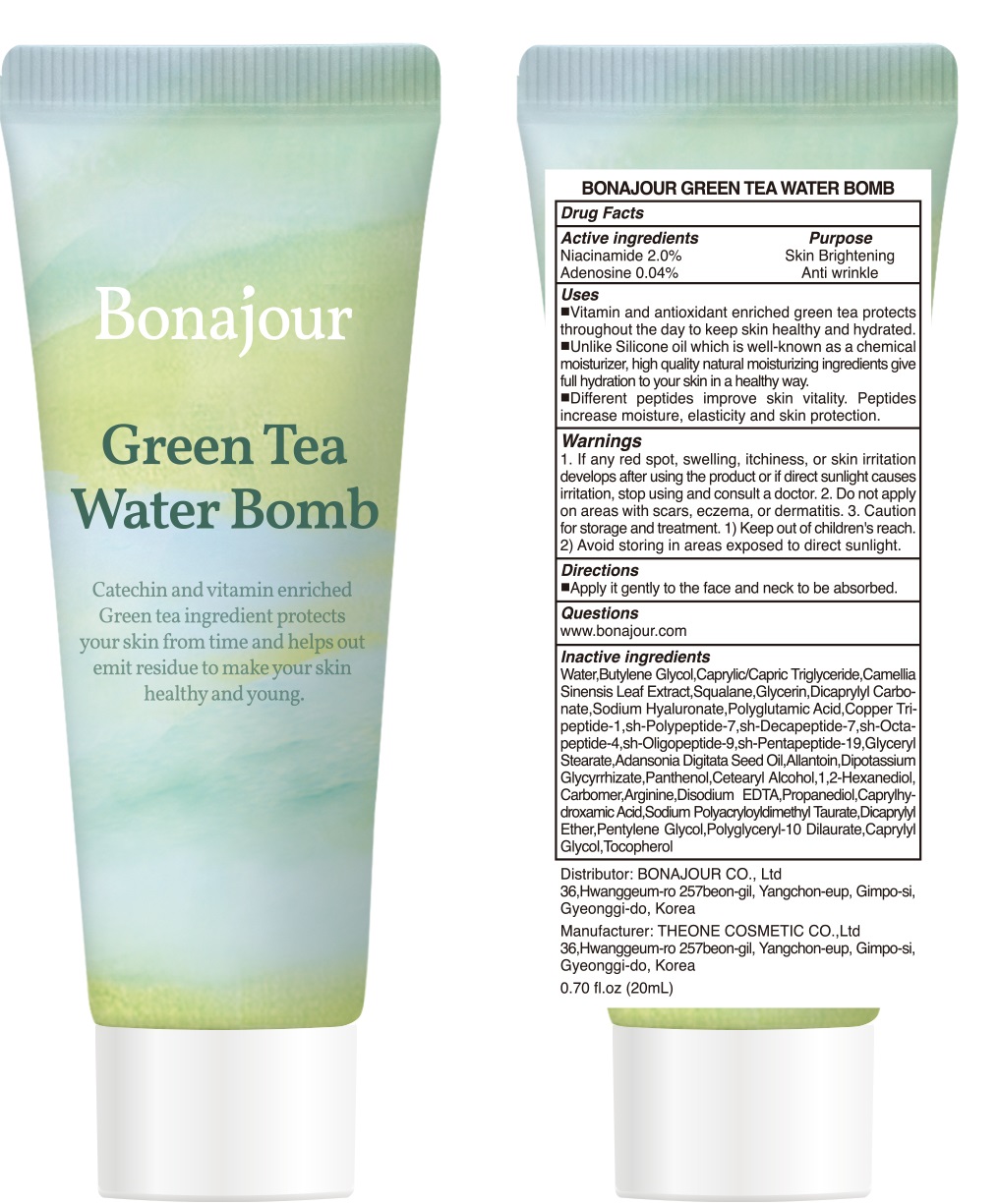 DRUG LABEL: BONAJOUR GREEN TEA WATER BOMB
NDC: 80706-010 | Form: CREAM
Manufacturer: BONAJOUR
Category: otc | Type: HUMAN OTC DRUG LABEL
Date: 20201109

ACTIVE INGREDIENTS: Niacinamide 2.0 g/100 mL; Adenosine 0.04 g/100 mL
INACTIVE INGREDIENTS: Water; Butylene Glycol

ACTIVE INGREDIENTS

Niacinamide 2.0%
Adenosine 0.04%

INACTIVE INGREDIENTS

Water,Butylene Glycol,Caprylic/Capric Triglyceride,Camellia Sinensis Leaf Extract,Squalane,Glycerin,Dicaprylyl Carbonate,Sodium Hyaluronate,Polyglutamic Acid,Copper Tripeptide-1,sh-Polypeptide-7,sh-Decapeptide-7,sh-Octapeptide-4,sh-Oligopeptide-9,sh-Pentapeptide-19,Glyceryl Stearate,Adansonia Digitata Seed Oil,Allantoin,Dipotassium Glycyrrhizate,Panthenol,Cetearyl Alcohol,1,2-Hexanediol,Carbomer,Arginine,Disodium EDTA,Propanediol,Caprylhydroxamic Acid,Sodium Polyacryloyldimethyl Taurate,Dicaprylyl ether,Pentylene Glycol,Polyglyceryl-10 Dilaurate,Caprylyl glycol,Tocopherol

PURPOSE

Skin Brightening
Anti wrinkle

WARNINGS

1. If any red spot, swelling, itchiness, or skin irritation develops after using the product or if direct sunlight causes irritation, stop using and consult a doctor.
2. Do not apply on areas with scars, eczema, or dermatitis.
3. Caution for storage and treatment. 1) Keep out of children's reach. 2) Avoid storing in areas exposed to direct sunlight.

KEEP OUT OF REACH OF CHILDREN

Keep out of children's reach.

Uses

■Vitamin and antioxidant enriched green tea protects throughout the day to keep skin healthy and hydrated.

■Unlike Silicone oil which is well-known as a chemical moisturizer, high quality natural moisturizing ingredients give full hydration to your skin in a healthy way.

■Different peptides improve skin vitality. Peptides increase moisture, elasticity and skin protection.

Directions

■ Apply it gently to the face and neck to be absorbed.

QUESTIONS

www.bonajour.com